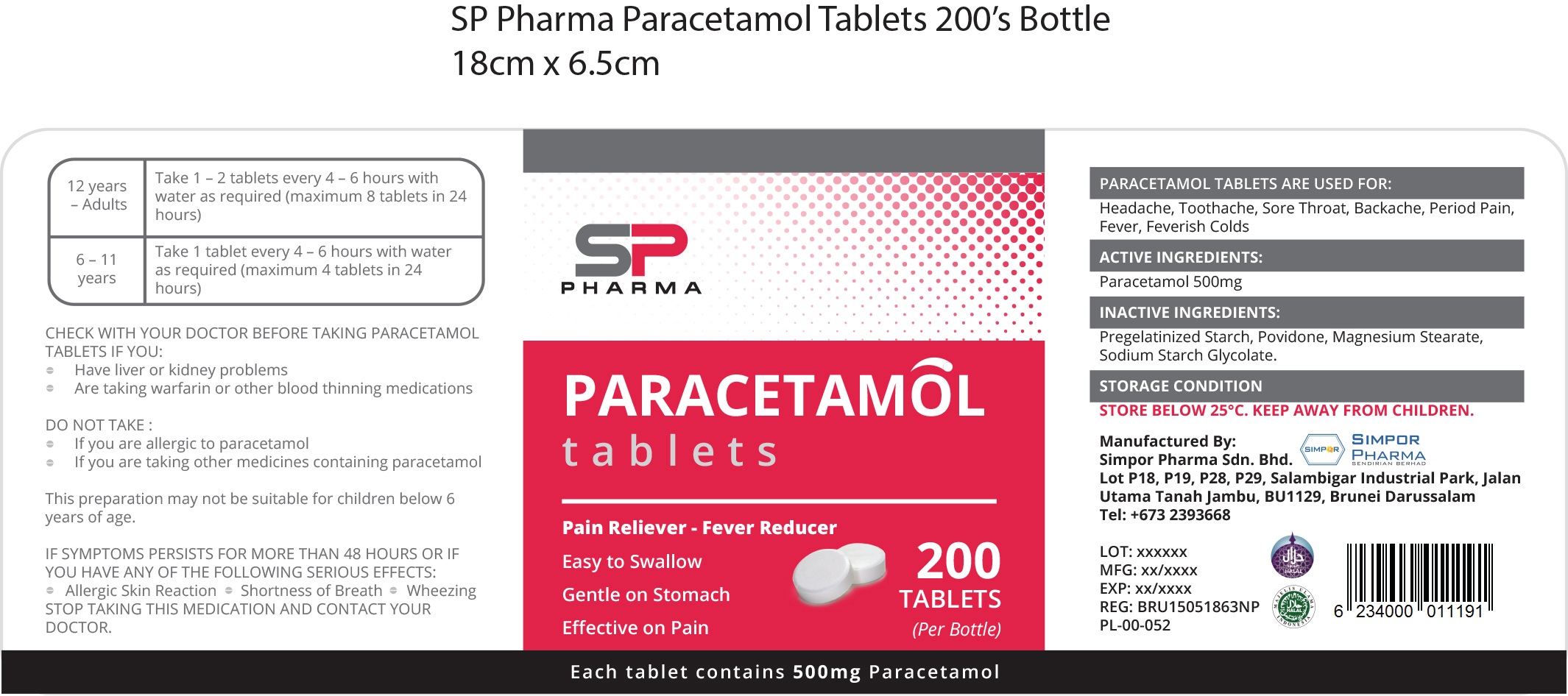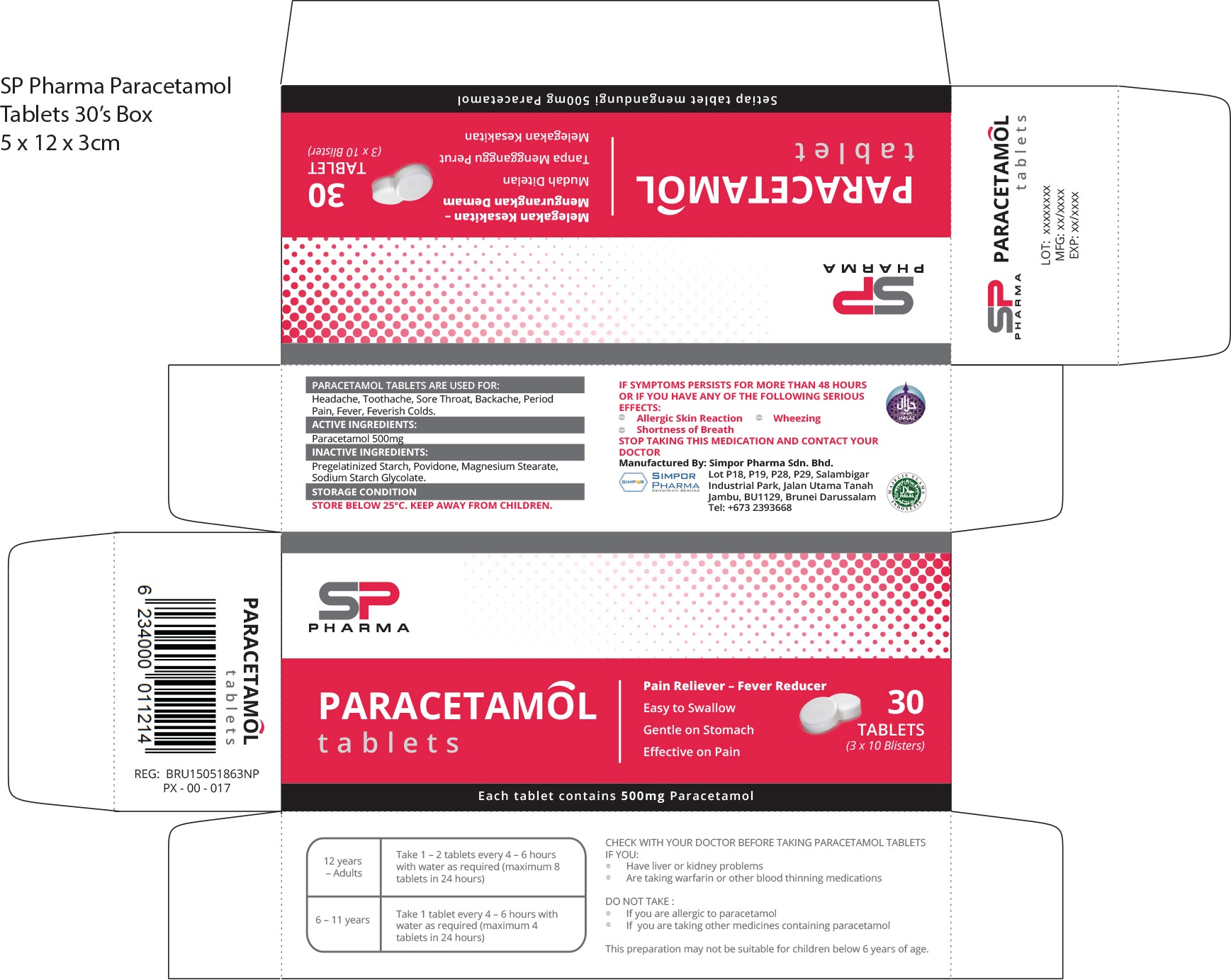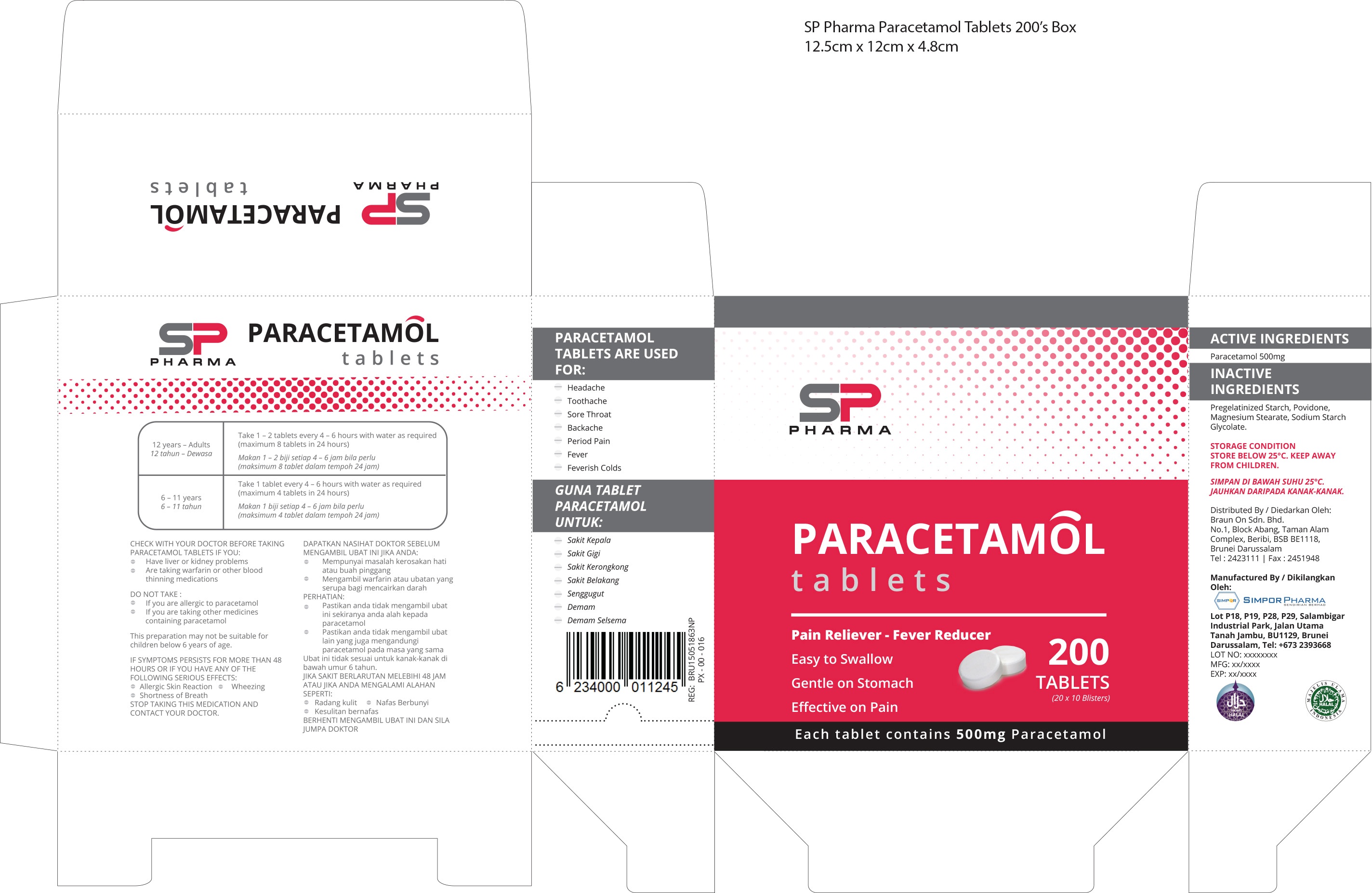 DRUG LABEL: SP Pharma
NDC: 70875-500 | Form: TABLET
Manufacturer: Simpor Pharma Sdn Bhd
Category: otc | Type: HUMAN OTC DRUG LABEL
Date: 20190130

ACTIVE INGREDIENTS: ACETAMINOPHEN 500 mg/583 mg
INACTIVE INGREDIENTS: STARCH, PREGELATINIZED CORN; POVIDONE; MAGNESIUM STEARATE; SODIUM STARCH GLYCOLATE TYPE A CORN

ACTIVE INGREDIENTS:

Paracetamol 500 mg

PURPOSE

PARACETAMOL TABLETS ARE USED FOR:

Headache, Toothache, Sore Throat, Backache, Period Pain,

Fever, Feverish Colds

WARNINGS

CHECK WITH YOUR DOCTOR BEFORE TAKING PARACETAMOL

TABLETS IF YOU:

-Have liver or kidney problems

-Are taking warfarin or toehr blood thinning medications

DO NOT TAKE:

-If you are allergic to paracetamol

-If you are taking other medicines containing paracetamol

This preparation may not be suitable for children below 6

years of age.

IF SYMPTOMS PERSIST FOR MORE THAN 48 HOURS OR IF

YOU HAVE ANY OF THE FOLLOWING SERIOUS EFFECTS:

-Allergic skin reaction -Shortness of Breath -Wheezing

STOP TAKING THIS MEDICATION AND CONTACT YOUR

DOCTOR

INDICATIONS AND USAGE

PARACETAMOL TABLETS ARE USED FOR:

Headache, Toothache, Sore Throat, Backache, Period Pain,

Fever, Feverish Colds

DOSAGE AND ADMINISTRATION

12 years - Adults

Take 1 -2 tablets every 4 - 6 hours with

water as required (maximum 8 tablets in 24

hours)

6-11 years

Take 1 tablet every 4 - 6 hours with water

as required (maximum 4 tablets in 24 hours)

INACTIVE INGREDIENTS:

Pregelatinized Starch, Povidone, Magnesium Stearate,

Sodium Starch Glycolate

STORAGE CONDITION

STORE BELOW 25C.

KEEP AWAY FROM CHILDREN